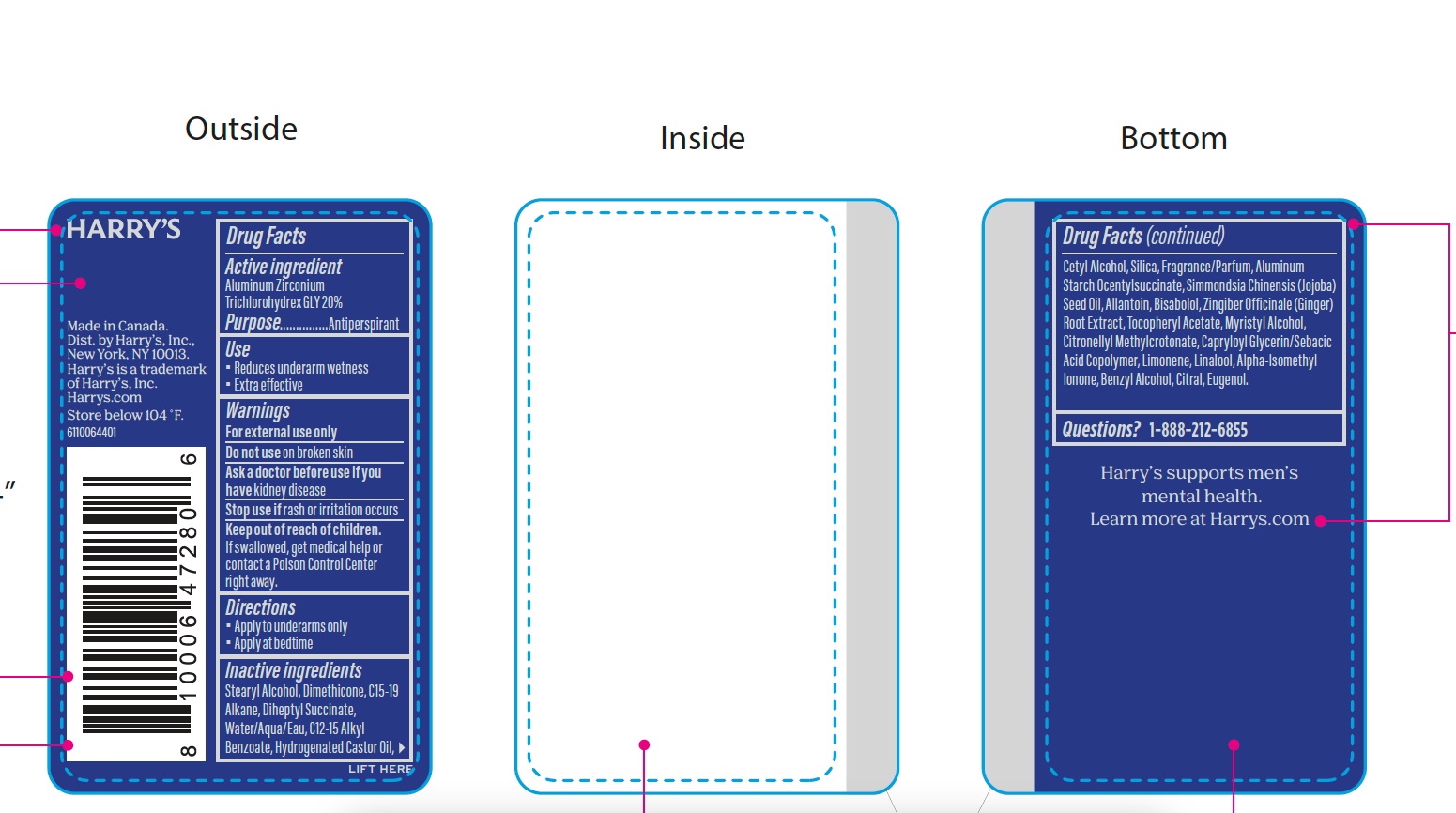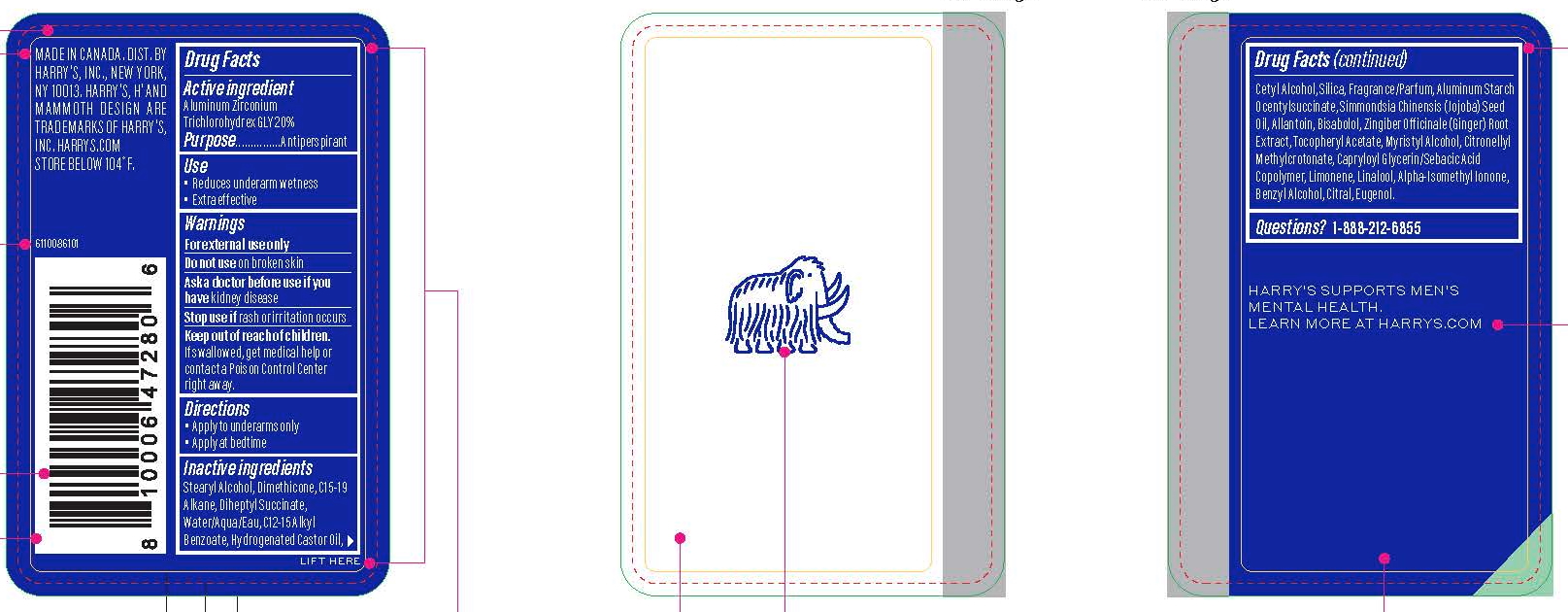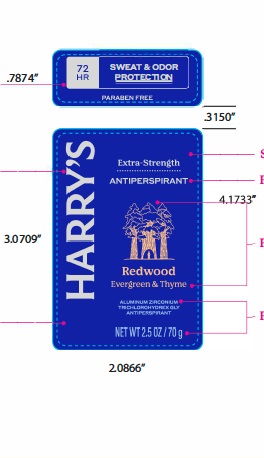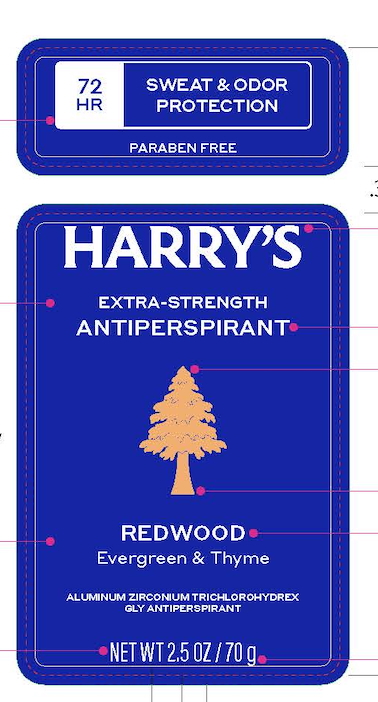 DRUG LABEL: Harrys Extra Strength Antiperspirant Redwood
NDC: 70533-013 | Form: STICK
Manufacturer: Harry's Inc.
Category: otc | Type: HUMAN OTC DRUG LABEL
Date: 20251208

ACTIVE INGREDIENTS: ALUMINUM ZIRCONIUM TRICHLOROHYDREX GLY 200 mg/1 g
INACTIVE INGREDIENTS: DIHEPTYL SUCCINATE; EUGENOL; WATER; C15-19 ALKANE; DIMETHICONE; JOJOBA OIL; .ALPHA.-BISABOLOL, (+/-)-; GINGER; ALLANTOIN; ISOMETHYL-.ALPHA.-IONONE; FRAGRANCE 13576; CAPRYLOYL GLYCERIN/SEBACIC ACID COPOLYMER (2000 MPA.S); LIMONENE, (+/-)-; .ALPHA.-TOCOPHEROL ACETATE; MYRISTYL ALCOHOL; CITRONELLYL METHYLCROTONATE; LINALOOL, (+/-)-; CITRAL; CETYL ALCOHOL; SILICON DIOXIDE; STEARYL ALCOHOL; HYDROGENATED CASTOR OIL; ALKYL (C12-15) BENZOATE; ALUMINUM STARCH OCTENYLSUCCINATE; BENZYL ALCOHOL

Extra Strength AP - Redwood

Active Ingredient

ALUMINUM ZIRCONIIUM TRICHLOROHYDREX GLY 20%

Purpose

Antiperspirant

Use

- Reduces underarm wetness.
- Extra effective.

Warnings

For external use only

Do not use on broken skin

Ask doctor before use if you have kidney disease

Stop use if rash or irritation occurs.

Keep out of reach of children. If swallowed, get medical help or contact a Poison Control Center right away.

Directions

- Apply to underarms only
- Apply at bedtime

Inactive Ingredients

STEARYL ALCOHOL, DIMETHICONE, C15-19 ALKANE, DIHEPTYL SUCCINATE, WATER/AQUA/EAU, C12-15 ALKYL BENZOATE, HYDROGENATED CASTOR OIL, CETYL ALCOHOL, SILICA, FRAGRANCE/PARFUM, ALUMINUM STARCH OCENTYLSUCCINATE, SIMMONDSIA CHINENSIS (JOJOBA) SEED OIL, ALLANTOIN, BISABOLOL, ZINGIBER OFFINCALE (GINGER) ROOT EXTRACT,
TOCOPHERYL ACETATE, MYRISTYL ALCOHOL, CITRONELLYL METHYLCROTONATE, CAPRYLOYL GLYCERIN/SEBACIC ACID COPOLYMER, LIMONENE, LINALOOL, ALPHA-ISOMETHYL IONONE, BENZYL ALCOHOL, CITRAL, EUGENOL.

Questions?: 1-888-212-6855

PACKAGE LABEL

NDC: 70533-013-25

PACKAGE LABEL

NDC: 70533-010-25